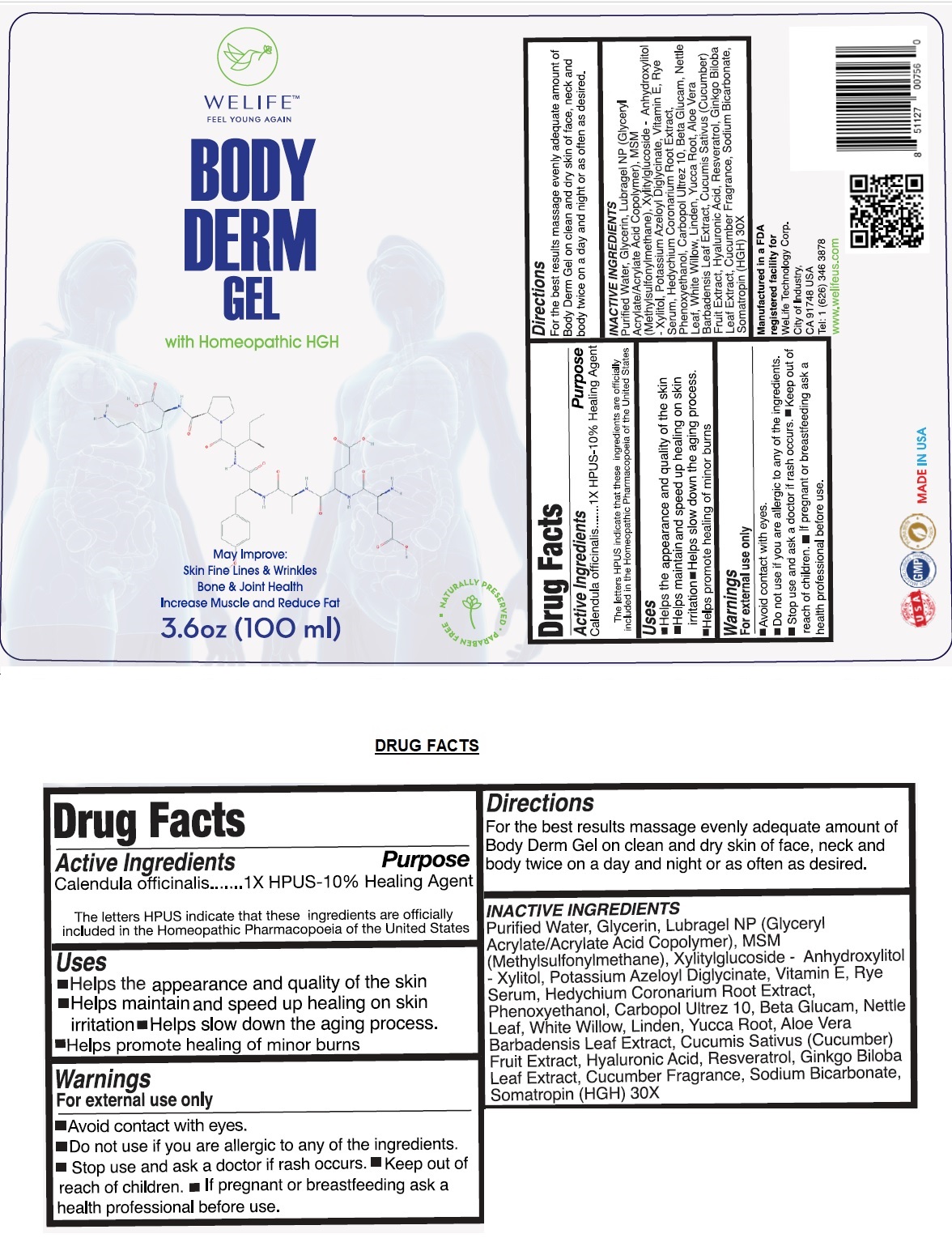 DRUG LABEL: BODY DERM
NDC: 73405-101 | Form: GEL
Manufacturer: Welife Technology Corp 
Category: homeopathic | Type: HUMAN OTC DRUG LABEL
Date: 20191122

ACTIVE INGREDIENTS: CALENDULA OFFICINALIS FLOWERING TOP 1 [hp_X]/100 mL
INACTIVE INGREDIENTS: WATER; GLYCERIN; DIMETHYL SULFONE; XYLITYLGLUCOSIDE; ANHYDROXYLITOL; XYLITOL; POTASSIUM AZELOYL DIGLYCINATE; .ALPHA.-TOCOPHEROL; HEDYCHIUM CORONARIUM ROOT; PHENOXYETHANOL; CARBOMER INTERPOLYMER TYPE A (ALLYL SUCROSE CROSSLINKED); TRANSFORMING GROWTH FACTOR BETA RECEPTOR TYPE 3; URTICA DIOICA SUBSP. DIOICA LEAF; SALIX ALBA WHOLE; LINDEN LEAF; YUCCA SCHIDIGERA ROOT; ALOE VERA LEAF; CUCUMBER; HYALURONIC ACID; RESVERATROL; GINKGO; SODIUM BICARBONATE; SOMATROPIN

BODY DERM GEL

Active Ingredients

Calendula officinalis ...1X HPUS-10%

The letters HPUS indicate that these ingredients are officially included in the Homeopathic Pharmacopoeia of the United States

Purpose

Healing Agent

Uses

•Helps the appearance and quality of the skin

•Helps maintain and speed up healing on skin irritation •Helps slow down the aging process.

•Helps promote healing of minor burns

Warnings

For external use only

•Avoid contact with eyes

•Do not use if you are allergic to any of the ingredients.

•Stop use and ask a doctor if rash occurs.

•If pregnant or breastfeeding ask a health professional before use.

•Keep out of reach of children.

Directions

For the best results massage evenly adequate amount of Body Derm Gel on clean and dry skin of face, neck and body twice on a day and night or as often as desired.

INACTIVE INGREDIENTS

Purified Water, Glycerin, Lubragel NP (Glyceryl Acrylate/Acrylic Acid Copolymer), MSM(Methylsulfonylmethane), Xylitylglucoside-Anydroxylitol-Xylitol, Potassium Azeloyl Diglycinate, Vitamin E, Rye Serum, Hedychium Coronarium Root Extract, Phenoxyethanol, Carbopol Ultrez 10, Beta Glucam, Nettle Leaf, White Willow, Linden, Yucca Root, Aloe Vera Barbadensis Leaf Extract, Cucumis Sativus (Cucumber) Fruit Extract, Hyaluronic Acid, Resveratrol, Ginkgo Biloba Leaf Extract, Cucumber Fragrance, Sodium Bicarbonate, Somatropin (HGH) 30X.

WELIFE™

FEEL YOUNG AGAIN

with Homeopathic HGH

May improve: Skin Fine Lines and Wrinkles

Bone & Joint Health

Increase Muscle and Reduce Fat

Manufactured in a FDA registered facility for

WeLife Technology Corp.

City of Industry

CA 91748 USA

Tel: 1 (626)346 3878

WWW.welifeus.com

MADE IN USA